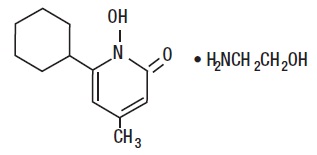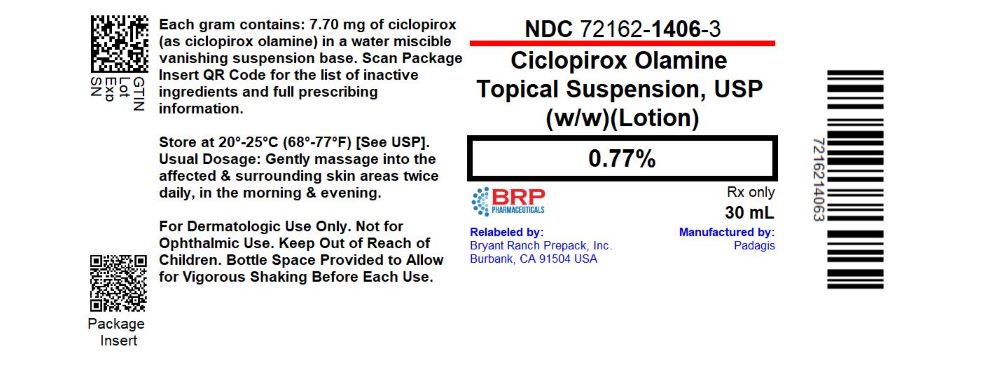 DRUG LABEL: Ciclopirox Olamine
NDC: 72162-1406 | Form: SUSPENSION
Manufacturer: Bryant Ranch Prepack
Category: prescription | Type: HUMAN PRESCRIPTION DRUG LABEL
Date: 20241224

ACTIVE INGREDIENTS: CICLOPIROX OLAMINE 7.70 mg/100 mL
INACTIVE INGREDIENTS: BENZYL ALCOHOL; CETYL ALCOHOL; LACTIC ACID, UNSPECIFIED FORM; LIGHT MINERAL OIL; MYRISTYL ALCOHOL; OCTYLDODECANOL; POLYSORBATE 60; WATER; SORBITAN MONOSTEARATE; STEARYL ALCOHOL

Ciclopirox Olamine Topical Suspension USP, 0.77%
(w/w) (Lotion)
Rx Only

FOR DERMATOLOGIC USE ONLY.

NOT FOR USE IN EYES.

DESCRIPTION

Ciclopirox Olamine Topical Suspension USP, 0.77% (w/w) (Lotion) is for topical use.

Each gram of Ciclopirox Olamine Topical Suspension USP, 0.77% (w/w) (Lotion) contains 7.70 mg of ciclopirox (as ciclopirox olamine) in a water miscible suspension base consisting of benzyl alcohol (1% as a preservative), cetyl alcohol, lactic acid, light mineral oil, myristyl alcohol, octyldodecanol, polysorbate 60, purified water, sorbitan monostearate, and stearyl alcohol.

Ciclopirox Olamine Topical Suspension USP, 0.77% (w/w) (Lotion) contains a synthetic, broad-spectrum, antifungal agent ciclopirox (as ciclopirox olamine).

The chemical name is 6-cyclohexyl-1-hydroxy-4-methyl-2(1H)-pyridone, 2-aminoethanol salt.

The CAS Registry Number is 41621-49-2.

Ciclopirox Olamine Topical Suspension USP, 0.77% (w/w) (Lotion) has a pH of 7. The chemical structure is:

CLINICAL PHARMACOLOGY

Ciclopirox is a broad-spectrum, antifungal agent that inhibits the growth of pathogenic dermatophytes, yeasts, and Malassezia furfur. Ciclopirox exhibits fungicidal activity in vitro against isolates of Trichophyton rubrum, Trichophyton mentagrophytes, Epidermophyton floccosum, Microsporum canis, and Candida albicans.

Pharmacokinetic studies in men with radiolabeled ciclopirox solution in polyethylene glycol 400, showed an average of 1.3% absorption of the dose when it was applied topically to 750 cm^2 on the back followed by occlusion for 6 hours.

The biological half-life was 1.7 hours and excretion occurred via the kidney. Two days after application only 0.01% of the dose applied could be found in the urine. Fecal excretion was negligible.

Autoradiographic studies with human cadaver skin showed that ciclopirox penetrates into the hair and through the epidermis and hair follicles into the sebaceous glands and dermis, while a portion of the drug remains in the stratum corneum.

In vitro penetration studies in frozen or fresh excised human cadaver and pig skin indicated that the penetration of ciclopirox olamine topical suspension, 0.77% is equivalent to that of ciclopirox (ciclopirox olamine) cream 0.77%. Therapeutic equivalence of cream and suspension formulations was also indicated by studies of experimentally induced guinea pig and human trichophytosis.

INDICATIONS AND USAGE

Ciclopirox Olamine Topical Suspension USP, 0.77% (w/w) (Lotion) is indicated for the topical treatment of the following dermal infections: tinea pedis, tinea cruris and tinea corporis due to Trichophyton rubrum, Trichophyton mentagrophytes, Epidermophyton floccosum, and Microsporum canis; cutaneous candidiasis (moniliasis) due to Candida albicans; and tinea (pityriasis) versicolor due to Malassezia furfur.

CONTRAINDICATIONS

Ciclopirox Olamine Topical Suspension USP, 0.77% (w/w) (Lotion) is contraindicated in individuals who have shown hypersensitivity to any of its components.

WARNINGS

General -

Ciclopirox Olamine Topical Suspension USP, 0.77% (w/w) (Lotion) is not for ophthalmic use. Keep out of reach of children.

PRECAUTIONS

If a reaction suggesting sensitivity or chemical irritation should occur with the use of Ciclopirox Olamine Topical Suspension USP, 0.77% (w/w) (Lotion), treatment should be discontinued and appropriate therapy instituted.

Information for Patients -

The patient should be told to:

1. Use the medication for the full treatment time even though signs/symptoms may have improved and notify the physician if there is no improvement after four weeks.
2. Inform the physician if the area of application shows signs of increased irritation (redness, itching, burning, blistering, swelling, oozing) indicative of possible sensitization.
3. Avoid the use of occlusive wrappings or dressings.

Carcinogenesis, Mutagenesis, Impairment of Fertility -

A carcinogenicity study in female mice dosed cutaneously twice per week for 50 weeks followed by a 6-month drug-free observation period prior to necropsy revealed no evidence of tumors at the application site.

The following in vitro and in vivo genotoxicity tests have been conducted with ciclopirox olamine: studies to evaluate gene mutation in the Ames Salmonella/Mammalian Microsome Assay (negative) and Yeast Saccharomyces Cerevisiae Assay (negative) and studies to evaluate chromosome aberrations in vivo in the Mouse Dominant Lethal Assay and in the Mouse Micronucleus Assay at 500 mg/kg (negative).

The following battery of in vitro genotoxicity tests were conducted with ciclopirox: a chromosome aberration assay in V79 Chinese Hamster Cells, with and without metabolic activation (positive); a gene mutation assay in the HGPRT - test with V79 Chinese Hamster Cells (negative); and a primary DNA damage assay (i.e., unscheduled DNA Synthesis Assay in A549 Human Cells (negative)). An in vitro Cell Transformation Assay in BALB/C3T3 Cells was negative for cell transformation. In an in vivo Chinese Hamster Bone Marrow Cytogenetic Assay, ciclopirox was negative for chromosome aberrations at 5000 mg/kg.

Pregnancy Category B -

Reproduction studies have been performed in the mouse, rat, rabbit, and monkey, via various routes of administration, at doses 10 times or more the topical human dose and have revealed no significant evidence of impaired fertility or harm to the fetus due to ciclopirox. There are, however, no adequate or well-controlled studies in pregnant women. Because animal reproduction studies are not always predictive of human response, this drug should be used during pregnancy only if clearly needed.

Nursing Mothers -

It is not known whether this drug is excreted in human milk. Caution should be exercised when Ciclopirox Olamine Topical Suspension USP, 0.77% (w/w) (Lotion) is administered to a nursing woman.

Pediatric Use -

Safety and effectiveness in pediatric patients below the age of 10 years have not been established.

ADVERSE REACTIONS

In the controlled clinical trial with 89 patients using ciclopirox olamine topical suspension and 89 patients using the vehicle, the incidence of adverse reactions was low. Those considered possibly related to treatment or occurring in more than one patient were pruritus, which occurred in two patients using ciclopirox olamine topical suspension and one patient using the suspension vehicle, and burning, which occurred in one patient using ciclopirox olamine topical suspension.

DOSAGE AND ADMINISTRATION

Gently massage Ciclopirox Olamine Topical Suspension USP, 0.77% (w/w) (Lotion) into the affected and surrounding skin areas twice daily, in the morning and evening. Clinical improvement with relief of pruritus and other symptoms usually occurs within the first week of treatment. If a patient shows no clinical improvement after four weeks of treatment with Ciclopirox Olamine Topical Suspension USP, 0.77% (w/w) (Lotion) the diagnosis should be redetermined. Patients with tinea versicolor usually exhibit clinical and mycological clearing after two weeks of treatment.

HOW SUPPLIED

Ciclopirox Olamine Topical Suspension USP, 0.77% (w/w) (Lotion) is available as follow:

NDC: 72162-1406-3: 30 mL in a BOTTLE

NDC: 72162-1406-6: 60 mL in a BOTTLE

Bottle space provided to allow for vigorous shaking before each use.

Repackaged/Relabeled by:
Bryant Ranch Prepack, Inc.
Burbank, CA 91504

STORAGE AND HANDLING

Store at 20° to 25° C (68° to 77° F) [see USP Controlled Room Temperature].

Manufactured By Padagis

Yeruham, Israel

Distributed By

Padagis

Allegan, MI 49010 • www.padagis.com

Rev 01-22

98L00 RC J1

PACKAGE LABEL

Ciclopirox Olamine 0.77% Lotion, USP 30 mL